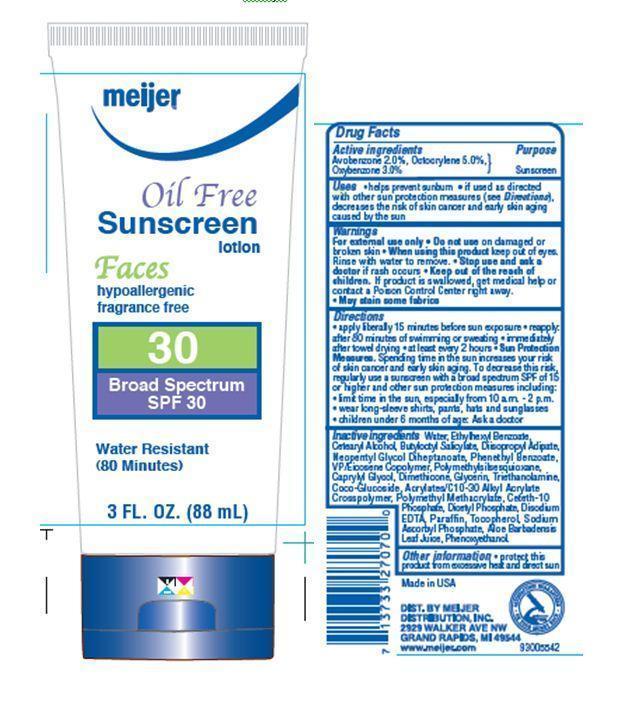 DRUG LABEL: MEIJER OIL FREE FACES SPF 30
NDC: 41250-036 | Form: LOTION
Manufacturer: Meijer Distribution Inc
Category: otc | Type: HUMAN OTC DRUG LABEL
Date: 20130710

ACTIVE INGREDIENTS: AVOBENZONE 2 g/100 g; OCTOCRYLENE 5 g/100 g; OXYBENZONE 3 g/100 g
INACTIVE INGREDIENTS: WATER; 2-ETHYLHEXYL BENZOATE; CETOSTEARYL ALCOHOL; BUTYLOCTYL SALICYLATE; DIISOPROPYL ADIPATE; NEOPENTYL GLYCOL DIHEPTANOATE; PHENETHYL BENZOATE; CAPRYLYL GLYCOL; DIMETHICONE; GLYCERIN; TROLAMINE; COCO GLUCOSIDE; DIHEXADECYL PHOSPHATE; EDETATE DISODIUM; PARAFFIN; TOCOPHEROL; SODIUM ASCORBYL PHOSPHATE; ALOE VERA LEAF; PHENOXYETHANOL

Drug Facts

Active ingredients
Avobenzone 2.0%

Octocrylene 5.0%

Oxybenzone 3.0%

Purpose

Sunscreen

Uses

- helps prevent sunburn
- if used as directed with other sun protection measures(see Directions), decreases the risk of skin cancer and early skin aging caused by the sun

Warnings

For external use only

Do not use

on damaged or broken skin

When using this product

keep out of eyes. Rinse with water to remove.

Stop use and ask a doctor

if rash occurs

Keep out of reach of children. If product is swallowed, get medical help or contact a Poison Control Center right away.

PRECAUTIONS

- May stain some fabrics.

Directions

- apply liberally 15 minutes before sun exposure
- reapply after 80 minutes of swimming or sweating
- immediately after towel drying
- at least every 2 hours
- Sun Protection Measures
- Spending time in the sun increases your risk of skin cancer and early skin aging. To decrease this risk, regularly use a sunscreen with a broad spectrum SPF of 15 or higher and other sun protection measures including:

- limit time in the sun, especially from 10 a.m.-2 p.m.
- wear long sleeve shirts, pants, hats and sunglasses
- children under 6 months of age: Ask a doctor.

Inactive ingredients

Water, Dicaprylyl Ether, PEG-8, VP/Hexadecene Copolymer, Dimethicone, Acrylates/C10-30 Alkyl Acrylate Crosspolymer, Triethanolamine, Polysorbate 20, Glycerin, Benzoic Acid, Disodium EDTA, Retinyl Palmitate, Tocopherol, Phenoxyethanol.

Principal Display Panel

meijer

Oil Free

Sunscreen Lotion

Faces

hypoallergenic

Fragrance Free

30

BROAD SPECTRUM SPF 30

Water Resistant

(80 Minutes)

3 FL. OZ.

(88 mL)

Other information

- protect the product from excessive heat and direct sun.